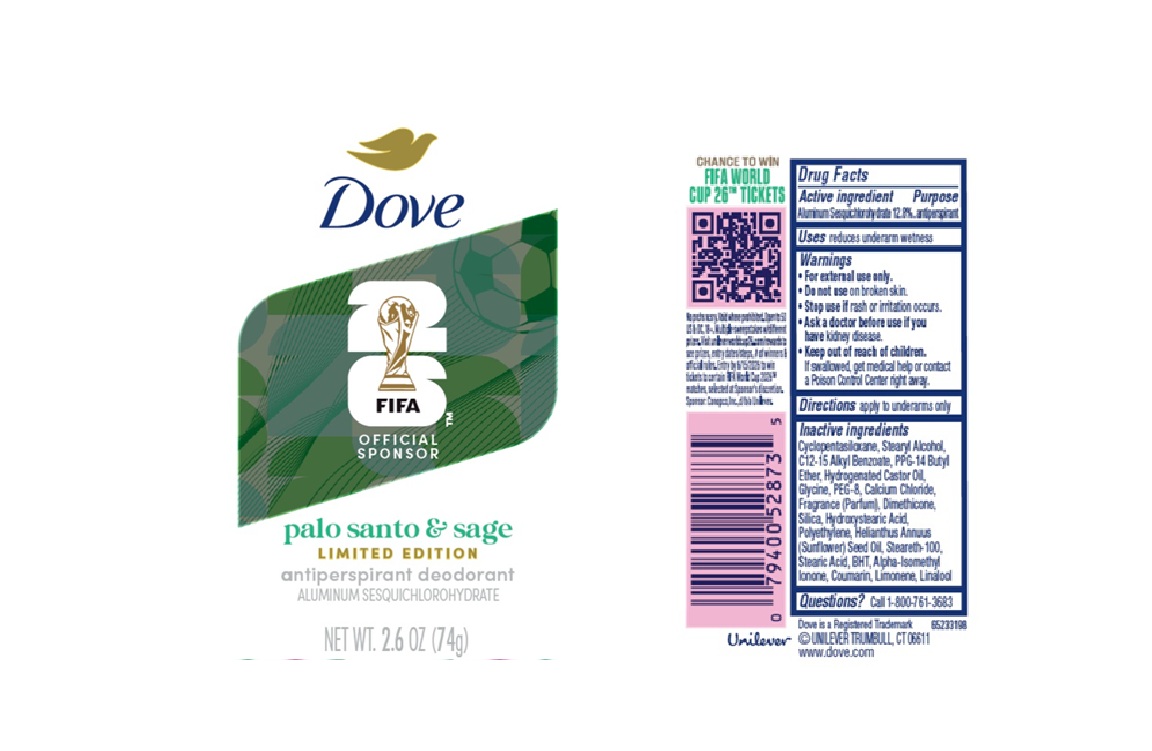 DRUG LABEL: Dove
NDC: 64942-2419 | Form: STICK
Manufacturer: Conopco d/b/a Unilever
Category: otc | Type: HUMAN OTC DRUG LABEL
Date: 20251219

ACTIVE INGREDIENTS: ALUMINUM SESQUICHLOROHYDRATE 12.8 g/100 g
INACTIVE INGREDIENTS: STEARETH-100; STEARIC ACID; HELIANTHUS ANNUUS (SUNFLOWER) SEED OIL; POLYETHYLENE; HYDROXYSTEARIC ACID; ALPHA-ISOMETHYL IONONE; LIMONENE, (+)-; COUMARIN; CYCLOPENTASILOXANE; GLYCINE; SILICA; BHT; DIMETHICONE; PPG-14 BUTYL ETHER; HYDROGENATED CASTOR OIL; LINALOOL; PEG-8; CALCIUM CHLORIDE; STEARYL ALCOHOL; C12-15 ALKYL BENZOATE

Dove FIFA 26 Palo Santo and Sage Limited Edition Antiperspirant Deodorant

DESCRIPTION

Dove FIFA 26 Palo Santo and Sage Limited Edition Antiperspirant Deodorant

ACTIVE INGREDIENT

Aluminum Sesquichlorohydrate 12.8%

PURPOSE

Antiperspirant

INDICATIONS AND USAGE

reduces underarm wetness

WARNINGS

• For external use only.
• Do not use on broken skin. • Stop use if rash or irritation occurs.• Ask a doctor before use if you have kidney disease. If swallowed, get medical help or contact a Poison Control Center right away.

• KEEP OUT OF REACH OF CHILDREN.

DOSAGE AND ADMINISTRATION

apply to underarms only

INACTIVE INGREDIENT

Cyclopentasiloxane, Stearyl Alcohol, C12-15 Alkyl Benzoate, PPG-14 Butyl Ether, Hydrogenated Castor Oil,
Glycine, PEG-8, Calcium Chloride, Fragrance (Parfum), Dimethicone, Silica, Hydroxystearic Acid, Polyethylene, Helianthus Annuus
(Sunflower) Seed Oil, Steareth-100, Stearic Acid, BHT, Alpha-Isomethyl Ionone, Coumarin, Limonene, Linalool

QUESTIONS

Call 1-800-761-3683